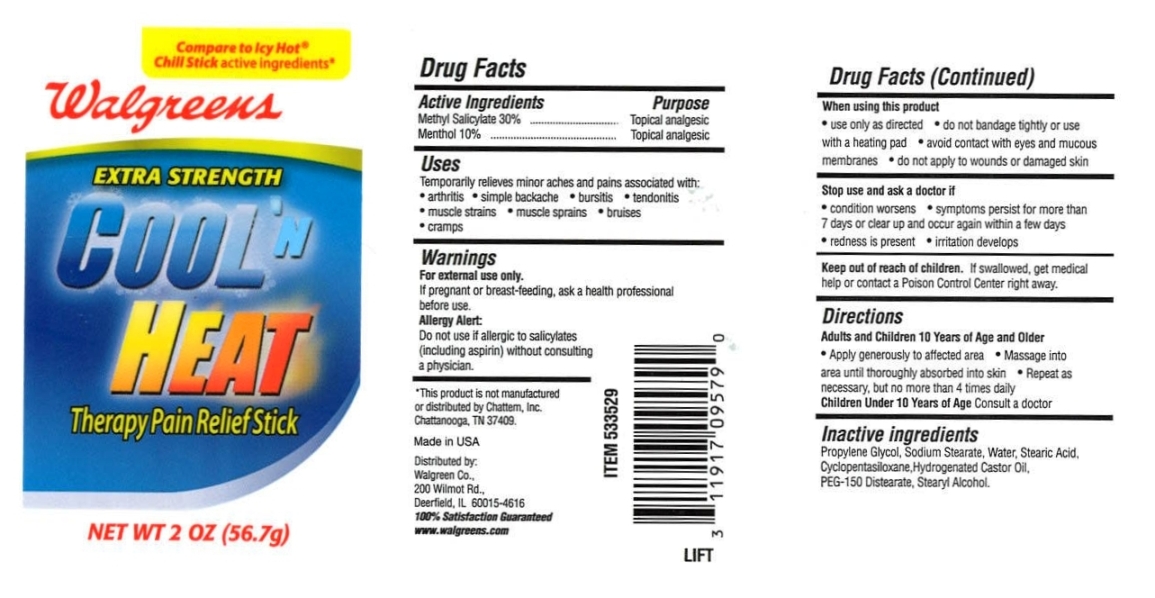 DRUG LABEL: Walgreens Cool N Heat
NDC: 10889-201 | Form: STICK
Manufacturer: VVF Kansas Services LLC
Category: otc | Type: HUMAN OTC DRUG LABEL
Date: 20091030

ACTIVE INGREDIENTS: methyl salicylate 30.0 1/1 1; menthol 10.0 1/1 1

Walgreens Cool N Heat (Methyl Salicylate and Menthol)

Active Ingredients

Methyl Salicylate 30%

Menthol 10%

Purpose

Topical Analgesic

Uses

Temporarily relieves minor aches and pains associated with:

- arthritis
- simple backache
- bursitis
- tendonitis
- muscle strains
- muscle sprains
- bruises
- cramps

Warnings

For external use only.

If pregnant or breast-feeding, ask a health professional before use.

Allergy Alert:

Do not use if allergic to salicylates (including aspirin) without consulting a physician.

When using this product

- use only as directed
- do not bandage tightly or use with a heating pad
- avoid contact with eyes and mucous membranes
- do not apply to wounds or damaged skin

Stop use and ask a doctor if

- condition worsens
- symptoms persist for more than 7 days or clear up and occur again within a few days
- redness is present
- irritation develops

Keep out of reach of children.

If swallowed, get medical help or contact a Poison Control Center right away.

Directions

Adults and Children 10 Years of Age or Older

- Apply generously to affected area
- Massage area until thoroughly absorbed into skin
- Repeat as necessary, but no more than 4 times daily

Children Under 10 Years of Age Consult a doctor

INACTIVE INGREDIENT

Propylene Glycol, Sodium Stearate, Water, Stearic Acid, Cyclopentasiloxane, Hydrogenated Castor Oil, PEG-150 Distearate, Stearyl Alcohol.

*This product is not manufactured or distributed by Chattem, Inc.Chattanooga, TN 37409.

Made in USA

Distributed by: Walgreen Co., 200 Wilmot Rd., Deerfield, IL 60015-4616

100% Satisfaction Guaranteed

www.wallgreens.com

PACKAGE LABEL

Compare to Icy Hot (R) Chill Stick active ingredients*

Walgreens

EXTRA STRENGTH

COOL 'N HEAT

Therapy Pain Relief Stick

NET WT 2 OZ (56.7G)

NDC 10889-201-11 (2 OZ)